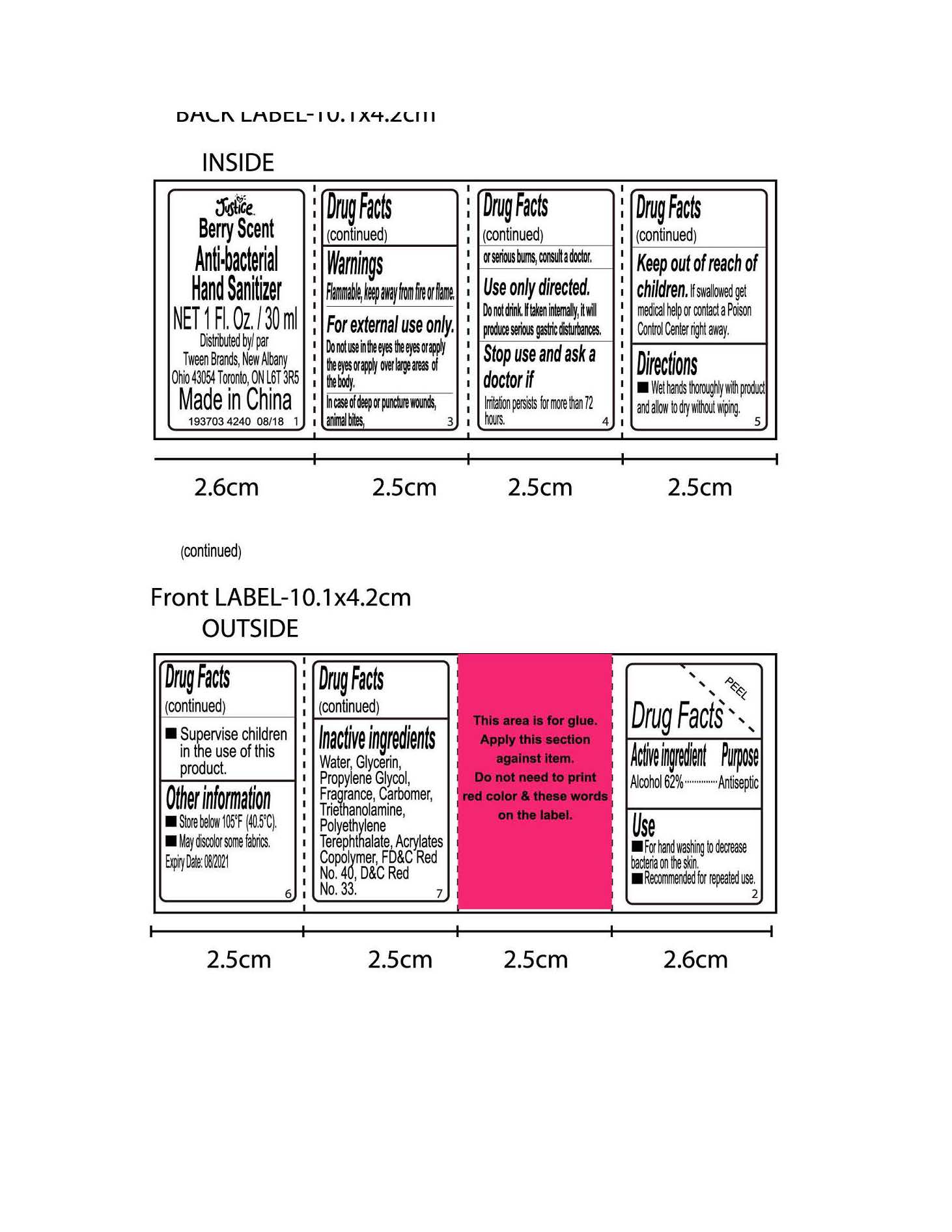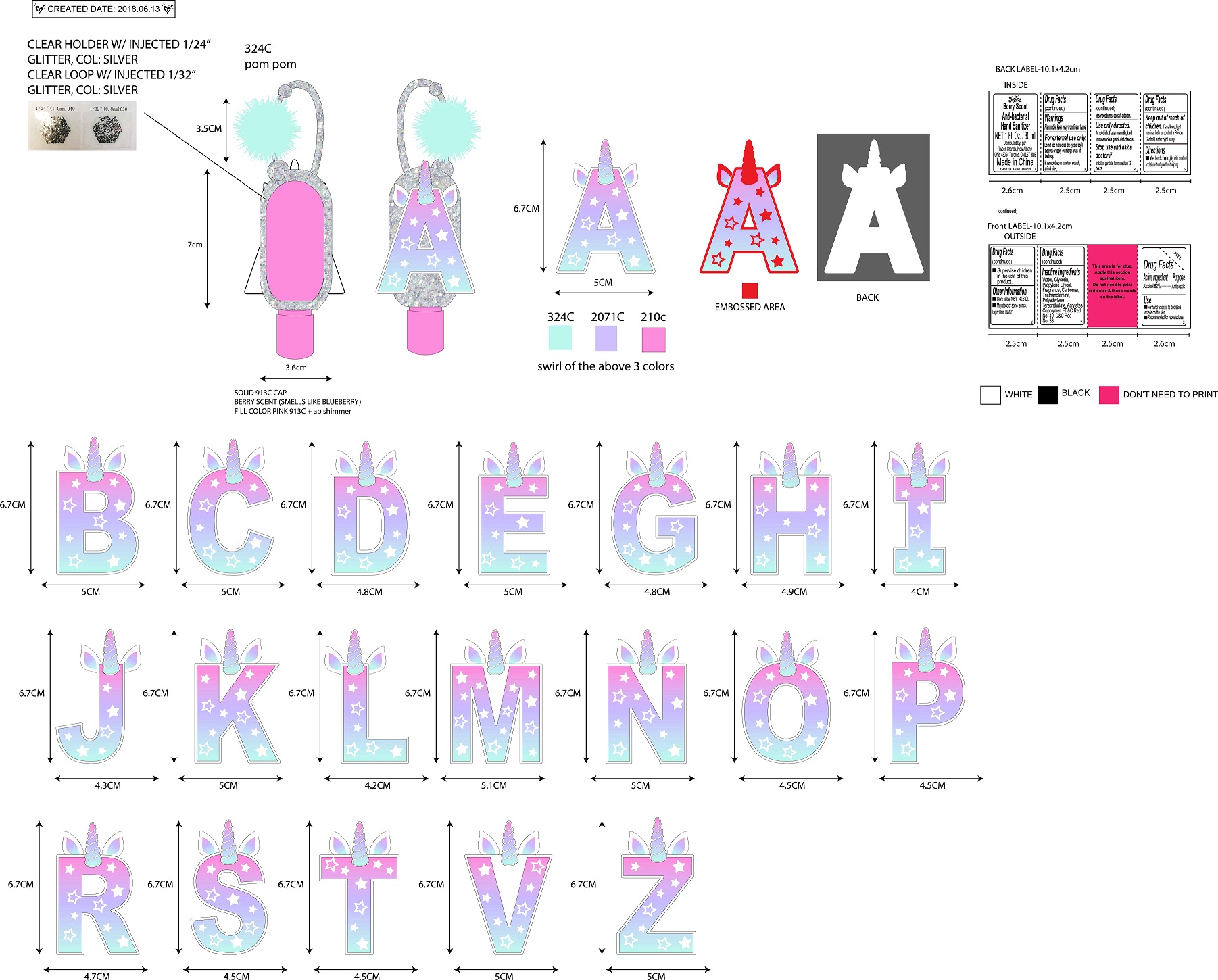 DRUG LABEL: Justice Berry Scented Anti-bacterial Hand Sanitizer
NDC: 60637-219 | Form: GEL
Manufacturer: Tween Brands, Inc.
Category: otc | Type: HUMAN OTC DRUG LABEL
Date: 20231025

ACTIVE INGREDIENTS: ALCOHOL 620 mg/100 mL
INACTIVE INGREDIENTS: WATER; GLYCERIN; PROPYLENE GLYCOL; CARBOXYPOLYMETHYLENE; 2,4-D-TROLAMINE; POLYETHYLENE TEREPHTHALATE (INTRINSIC VISCOSITY 0.40-0.70); BUTYL ACRYLATE/METHYL METHACRYLATE/METHACRYLIC ACID COPOLYMER (18000 MW); FD&C RED NO. 40; D&C RED NO. 33

Justice Berry Scented Antibaacterial Hand Sanitizer

Active Ingredient

Alcohol 62%

Purpose

Antiseptic

Use

For hand washing to decrease bacteria on the skin

Recommended for repeated use

Directions

Wet hands thoroughly with product and allow to dry without wiping

Warnings

Flammable, keep away from fire or flame

For external use only. Do not use in the eyes the eyes or apply the eyes or apply over large areas of the body

In case of deep or puncture wounds, animal bites, or serious burns, consult a doctor

Use only directed. Do not drink. If taken internally, it will produce serious gastric disturbance

Stop use and ask a doctor if irritation persists for more than 72 hours

Keep out of reach of children

If swallowed gel medical helpo r contact a Poison Control Center right away

Supervise children in the use of this product

Inactive ingredients

Water, glycerin, propylene glycol, fragrance, carbomer, triethanolamine, polyethylene terephthalate, acrylates copolymer, FD&C red No. 40, D&C Red No. 33